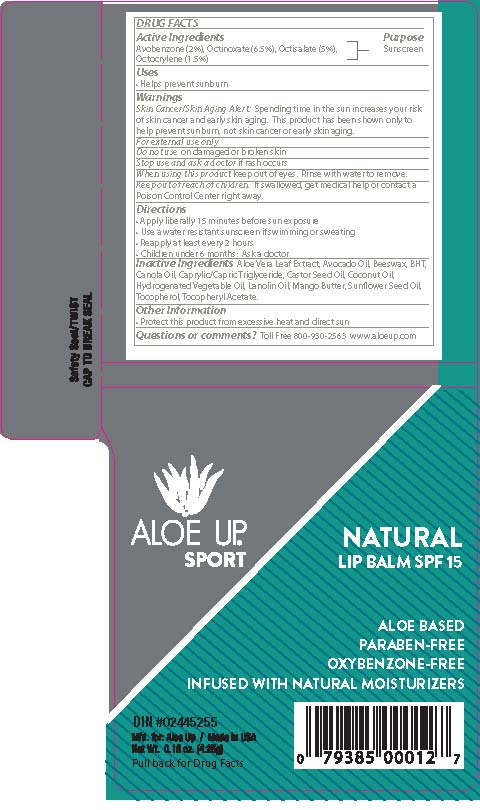 DRUG LABEL: ALOE UP SPORT NATURAL BALM
NDC: 61477-219 | Form: STICK
Manufacturer: Aloe Care International, LLC
Category: otc | Type: HUMAN OTC DRUG LABEL
Date: 20260130

ACTIVE INGREDIENTS: AVOBENZONE 2 g/100 g; OCTINOXATE 6.5 g/100 g; OCTISALATE 5 g/100 g; OCTOCRYLENE 1.5 g/100 g
INACTIVE INGREDIENTS: ALOE VERA LEAF; AVOCADO OIL; YELLOW WAX; BUTYLATED HYDROXYTOLUENE; CANOLA OIL; MEDIUM-CHAIN TRIGLYCERIDES; CASTOR OIL; COCONUT OIL; HYDROGENATED SOYBEAN OIL; LANOLIN; MANGIFERA INDICA SEED BUTTER; SUNFLOWER OIL; TOCOPHEROL; .ALPHA.-TOCOPHEROL ACETATE

ALOE UP SPORT - NATURAL LIP SUNSCREEN SPF 15 (61477-219)

ACTIVE INGREDIENTS

Avobenzone (2%)

Octinoxate (6.5%)

Octisalate (5%)

Octocrylene (1.5%)

PURPOSE

SUNSCREEN

USES

- HELPS PREVENT SUNBURN.

DIRECTIONS

- APPLY LIBERALLY 15 MINUTES BEFORE SUN EXPOSURE.
- USE A WATER RESISTANT SUNSCREEN IF SWIMMING OR SWEATING.
- REAPPLY AT LEAST EVERY 2 HOURS.
- CHILDREN UNDER 6 MONTHS: ASK A DOCTOR.

Keep out of reach of children. If swallowed, get medical help or contact a Poison Control Center right away.

WARNINGS

Skin Cancer/Skin Aging Alert: Spending time in the sun increases your risk of skin cancer and early skin aging. This product has been shown only to help prevent sunburn, not skin cancer or early skin aging.

For external use only

Do not use on damaged or broken skin

Stop use and ask a doctor if rash occurs

When using this product keep out of eyes. Rinse with water to remove.

INACTIVE INGREDIENTS

Aloe Vera Leaf Extract, Avocado Oil, Beeswax, BHT, Canola Oil, Caprylic/Capric Triglyceride, Castor Seed Oil, Coconut Oil,
Hydrogenated Vegetable Oil, Lanolin Oil, Mango Butter, Sunflower Seed Oil, Tocopherol, Tocopheryl Acetate.

OTHER INFORMATION

- Protect this product from excessive heat and direct sun

QUESTIONS OR COMMENTS?

Toll Free 800-950-2563 www.aloeup.com